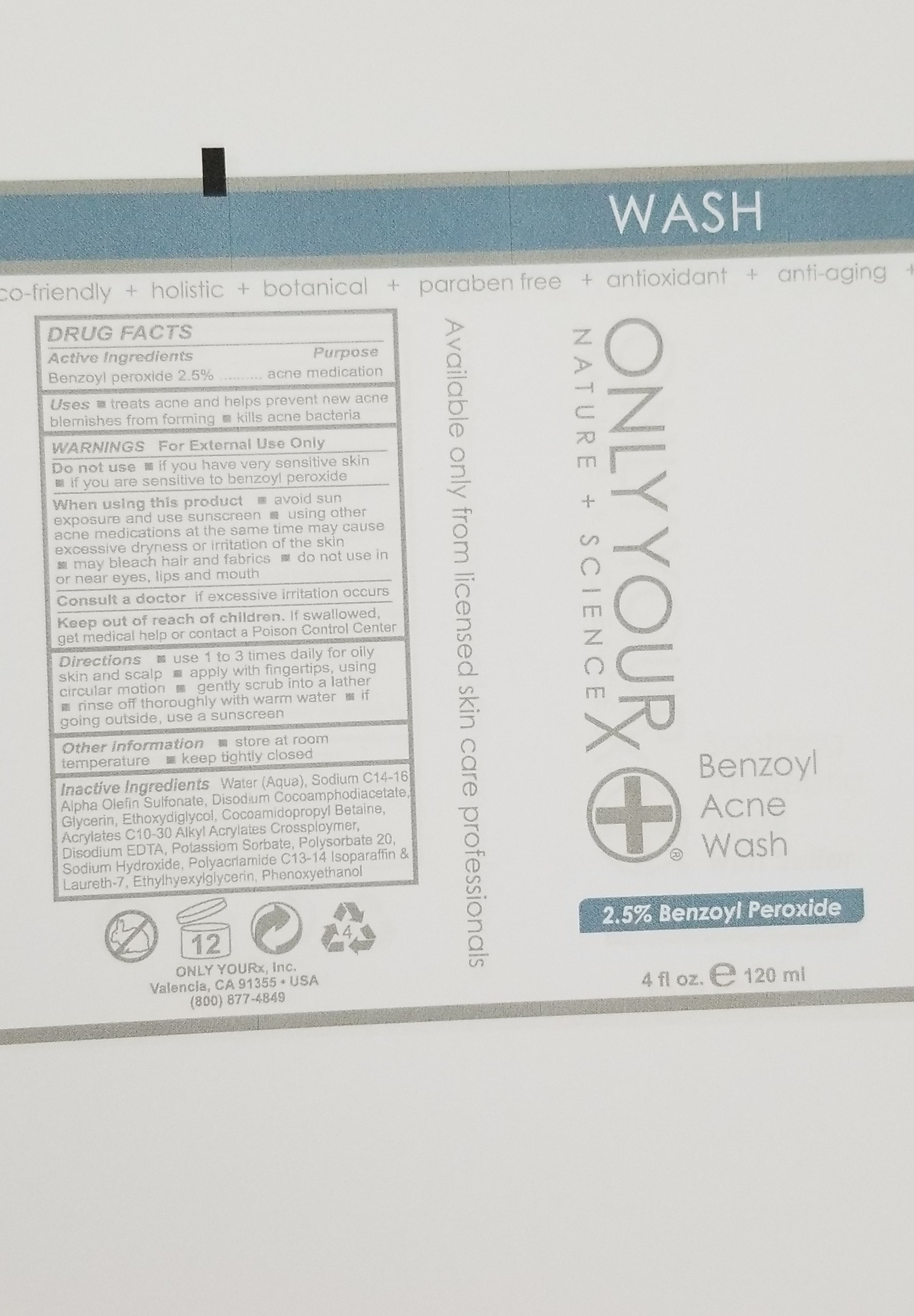 DRUG LABEL: Benzoyl Acne Wash -2.5% Benzoyl Peroxide
NDC: 70367-009 | Form: SOAP
Manufacturer: Only Yourx, Inc.
Category: otc | Type: HUMAN OTC DRUG LABEL
Date: 20200123

ACTIVE INGREDIENTS: BENZOYL PEROXIDE 2.5 g/100 mL
INACTIVE INGREDIENTS: ETHYLHEXYLGLYCERIN; PHENOXYETHANOL; POTASSIUM SORBATE; POLYSORBATE 20; C13-14 ISOPARAFFIN; LAURETH-7; GLYCERIN; ETHOXYDIGLYCOL BEHENATE; COCAMIDOPROPYL BETAINE; (C10-C30)ALKYL METHACRYLATE ESTER; MAGNESIUM DISODIUM EDTA; WATER; SODIUM C14-16 OLEFIN SULFONATE; DISODIUM COCOAMPHODIACETATE; SODIUM HYDROXIDE; POLYACRYLAMIDE (10000 MW)

DOSAGE AND ADMINISTRATION

Directions: use 1 to 3 times daily for oily skin and scalp; apply with fingertips, using circular motion; gently scrub into a lather; rinse off thoroughly with warm water; if going outside, use a sunscreen

Warnings: For External Use Only

INACTIVE INGREDIENT

Inactive Ingredients: Water, Sodium C14-16 Alpha Olefin Sulfonate, Disodium Cocoamyphodiacetate, Glycerin, Ethoxydiglycol, Cocoamidopropyl Betaine, Acrylates C10-20 Alkyl Acrylates Crosspolymer, Disodium EDA, Potassium Sorbate, Polysorbate 20, Sodium Hydroxide, Polyacrylmide, C13-14 Isoparaffin, Laureth-7, Ethylhexylglycerin, Phenoxyethanol

INDICATIONS AND USAGE

Uses: treats acne and helps prevent new acne blemishes from forming; kills acne bacteria

PURPOSE

Treats acne and prevents new acne blemishes from forming

Active Ingredients: Benzoyl Peroxide 2.5%

Keep out of reach of children. If swallowed, get medical help or contact a Poison Control Center

Consult a doctor: if excessive irritation occurs

Other Information: store at room temperature; keep tightly closed